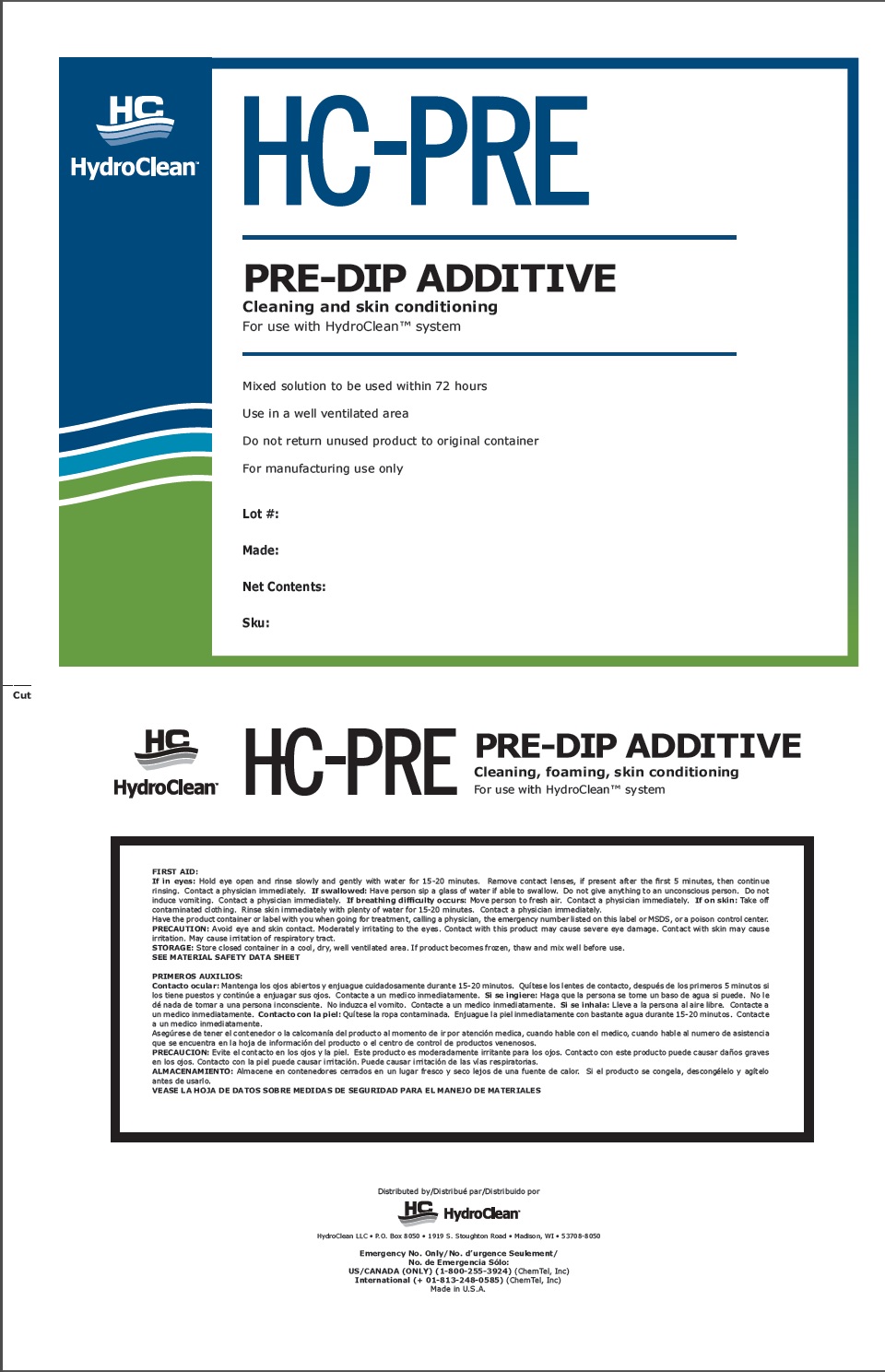 DRUG LABEL: HC-PRE
NDC: 86006-0001 | Form: LIQUID
Manufacturer: HydroClean
Category: animal | Type: OTC ANIMAL DRUG LABEL
Date: 20130701

ACTIVE INGREDIENTS: MYRISTAMINE OXIDE 300 g/1 L

HC-PRE

INDICATIONS AND USAGE

Pre-Dip Additive

Cleaning, foaming, skin conditioning

For use with HydroClean system

Mixed solution to be used within 72 hours

Use in a well ventilated area

Do not return unused product to original container

For Manufacturing Use Only

PRECAUTIONS

FIRST AID:
If in eyes: Hold eye open and rinse slowly and gently with water for 15-20 minutes. Remove contact lenses, if present after the first 5 minutes, then continue
rinsing. Contact a physician immediately.

If swallowed: Have person sip a glass of water if able to swallow. Do not give anything to an unconscious person. Do not
induce vomiting. Contact a physician immediately. If breathing difficulty occurs: Move person to fresh air. Contact a physician immediately.

If breathing difficulty occurs: Move person to fresh air. Contact a physician immediately.

If on skin: Take off contaminated clothing. Rinse skin immediately with plenty of water for 15-20 minutes. Contact a physician immediately.
Have the product container or label with you when going for treatment, calling a physician, the emergency number listed on this label or MSDS, or a poison control center.

PRECAUTION: Avoid eye and skin contact. Moderately irritating to the eyes. Contact with this product may cause severe eye damage. Contact with skin may cause
irritation. May cause irritation of respiratory tract.

STORAGE: Store closed container in a cool, dry, well ventilated area. If product becomes frozen, thaw and mix well before use.

SEE MATERIAL SAFETY DATA SHEET

PACKAGE LABEL

Enter section text here